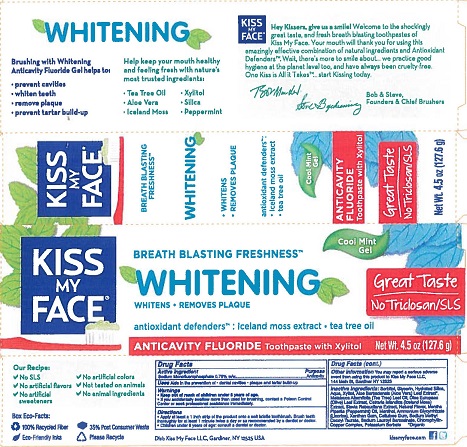 DRUG LABEL: Kiss My Face
NDC: 65364-400 | Form: GEL, DENTIFRICE
Manufacturer: Kiss My Face, LLC
Category: otc | Type: HUMAN OTC DRUG LABEL
Date: 20190218

ACTIVE INGREDIENTS: SODIUM MONOFLUOROPHOSPHATE 0.76 g/100 g
INACTIVE INGREDIENTS: PEPPERMINT OIL; SORBITOL; WATER; TEA TREE OIL; OLEA EUROPAEA LEAF; SODIUM METHYL COCOYL TAURATE; SODIUM LAUROYL SARCOSINATE; AMMONIUM GLYCYRRHIZATE; XANTHAN GUM; CARBOXYMETHYLCELLULOSE SODIUM, UNSPECIFIED FORM; STEVIA REBAUDIUNA LEAF; MENTHOL; CETRARIA ISLANDICA SUBSP. ISLANDICA; SODIUM COPPER CHLOROPHYLLIN; POTASSIUM SORBATE; GLYCERIN; HYDRATED SILICA; XYLITOL; ALOE VERA LEAF

Kiss My Face Whitening Toothpaste

Drug Facts

Active ingredient

Sodium monofluorphosphate 0.76% w/w

Purpose

Anticavity

Uses

Aids in the prevention of

- dental cavities
- plaque and tartar build-up

Warnings

- Keep out of reach of children.
- If you accidentally swallow more than used for brushing, contact a Poison Control Center or seek professional assistance immediately.

Directions

- Apply at least a 1 inch strip of the product onto a soft bristle toothbrush. Brush teeth thoroughly for at least 1 minute twice a day or as recommended by a dentist or doctor.
- Children under 6 years of age: consult a dentist or doctor

Other information

You may report a serious adverse event from using this product to Kiss My Face, LLC, 144 Main Street, Gardiner, NY 12525.

INACTIVE INGREDIENT

Inactive ingredients: Sorbitol, Glycerin, Hydrated Silica, Aqua, Xylitol, Aloe Barbadensis (Aloe Vera) Leaf Extract*, Melaleuca Alternifolia (Tea Tree) Leaf Oil, Olea Europaea (Olive) Leaf Extract, Cetraria Islandica (Iceland Moss) Extract, Stevia Rebaudiana Extract, Natural Flavor, Mentha Piperita (Peppermint) Oil, Menthol, Ammonium Glycyrrhizate (Licorice), Xanthan Gum, Cellulose Gum, Sodium Methyl Cocoyl Taurate, Sodium Lauroyl Sarcosinate, Chlorophyllin-Copper Complex, Potassium Sorbate

*Organic

Dist. Kiss My Face LLC, Gardiner, NY 12525 USA

PACKAGE LABEL

KISS MY FACE®

BREATH BLASTING FRESHNESS™

WHITENING ANTICAVITY FLUORIDE Toothpaste with Xylitol

WHITENS • REMOVES PLAQUE

Cool Mint Gel

Great Taste - No Triclosan/SLS

antioxidant defenders™: Iceland moss extract • tea tree oil

Net Wt. 4.5 oz (127.6 g)